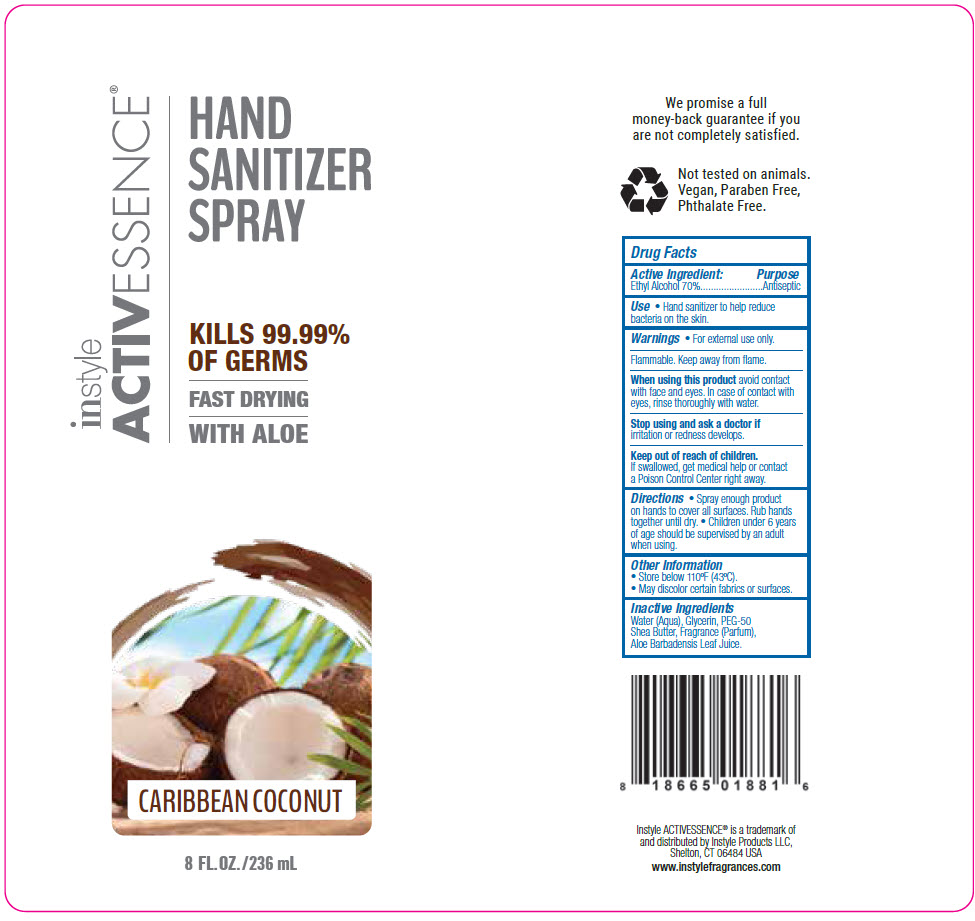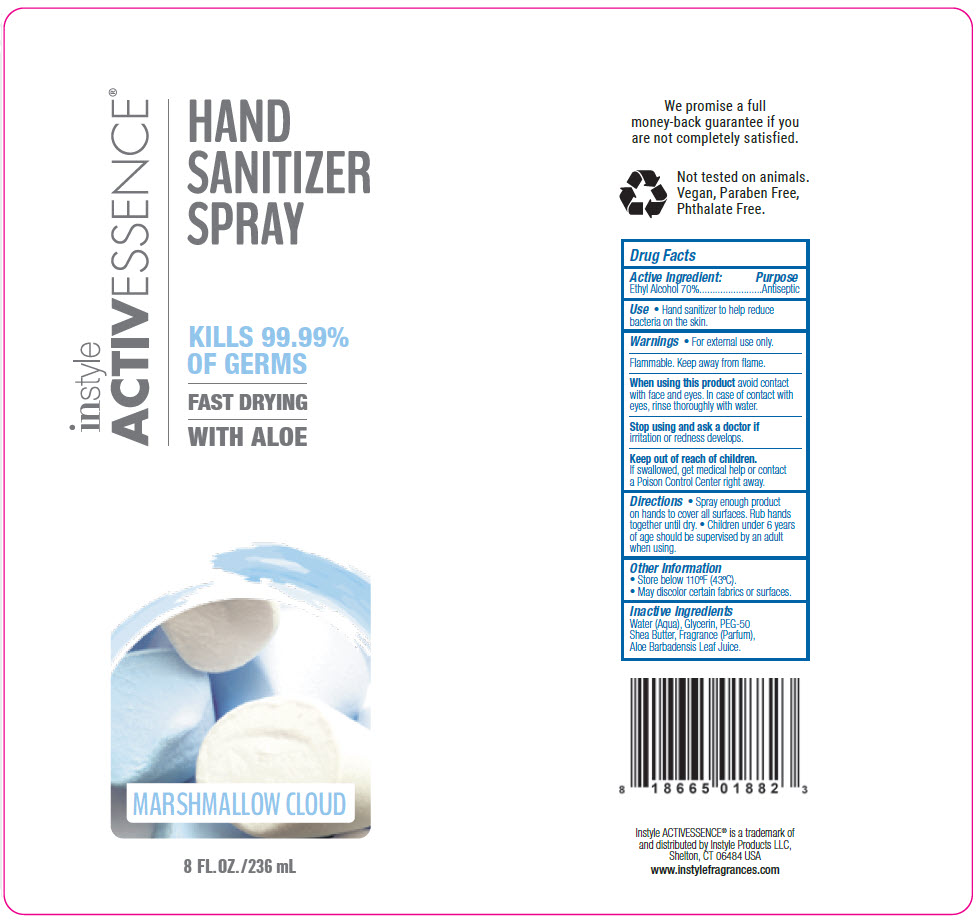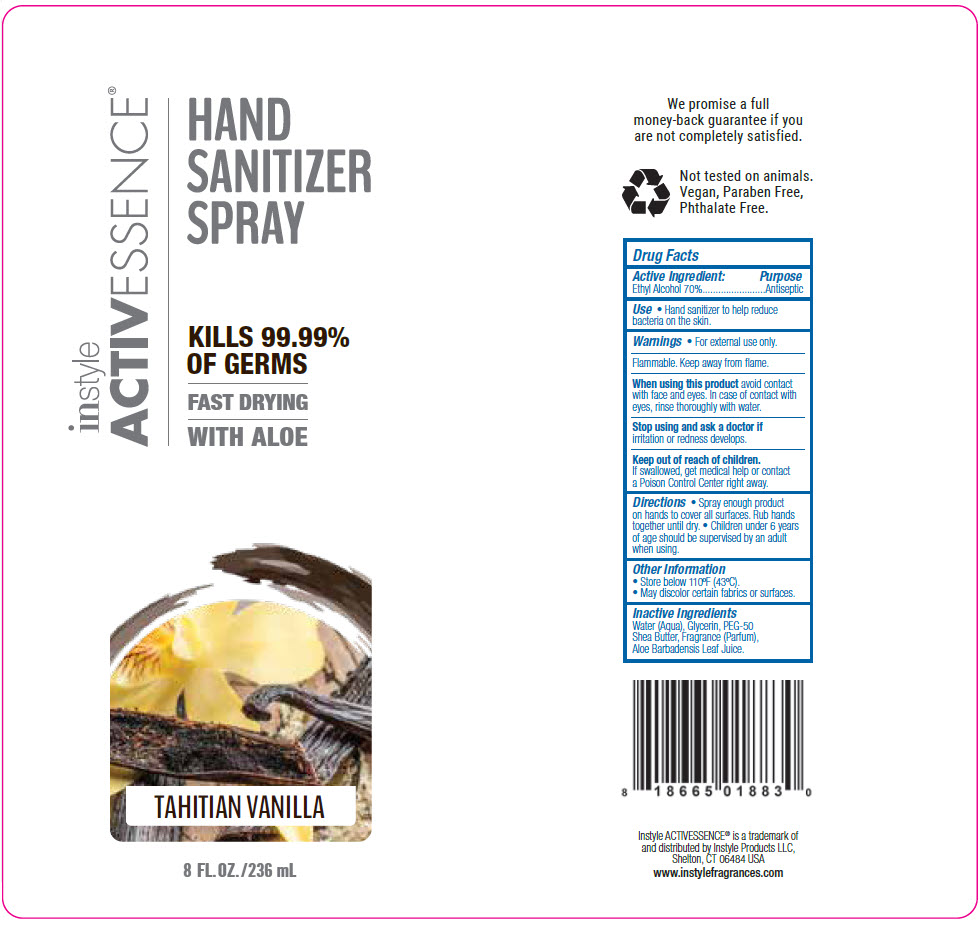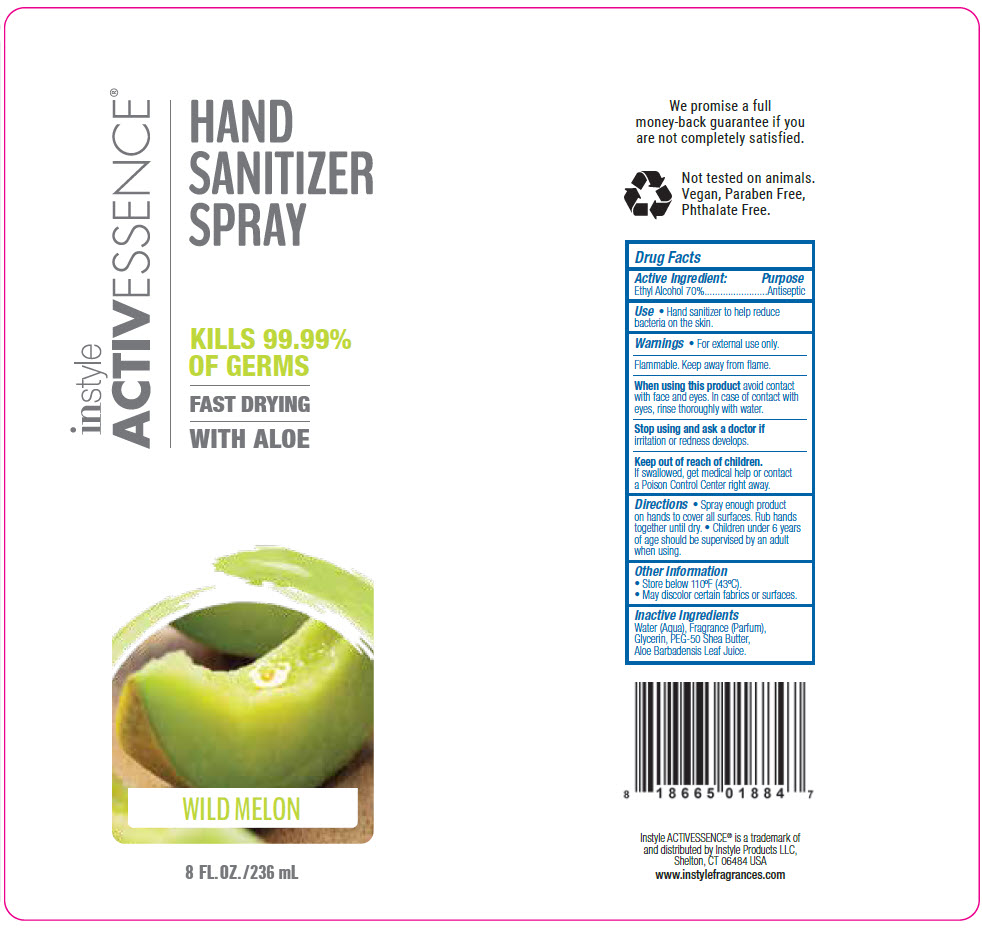 DRUG LABEL: Activessence 
NDC: 74445-630 | Form: SPRAY
Manufacturer: INSTYLE PRODUCTS LLC.
Category: otc | Type: HUMAN OTC DRUG LABEL
Date: 20220407

ACTIVE INGREDIENTS: ALCOHOL 70 mL/100 mL
INACTIVE INGREDIENTS: Glycerin; PEG-50 Shea Butter; ALOE VERA LEAF

Activessence®

Drug Facts

Active Ingredient

Ethyl Alcohol 70%

Purpose

Antiseptic

Use

- Hand sanitizer to help reduce bacteria on the skin.

Warnings

- For external use only.

Flammable. Keep away from flame.

When using this product avoid contact with face and eyes. In case of contact with eyes, rinse thoroughly with water.

STOP USE

Stop using and ask a doctor if irritation or redness develops.

Keep out of reach of children. If swallowed, get medical help or contact a Poison Control Center right away.

Directions

- Spray enough product on hands to cover all surfaces. Rub hands together until dry.
- Children under 6 years of age should be supervised by an adult when using.

Other Information

- Store below 110°F (43°C).
- May discolor certain fabrics or surfaces.

Inactive Ingredients

Water (Aqua), Glycerin, PEG-50 Shea Butter, Fragrance (Parfum), Aloe Barbadensis Leaf Juice.

distributed by Instyle Products LLC,
Shelton, CT 06484 USA

PRINCIPAL DISPLAY PANEL - 236 mL Bottle Label - Caribbean Coconut

instyle
ACTIVESSENCE®

HAND
SANITIZER
SPRAY

KILLS 99.99%
OF GERMS

FAST DRYING
WITH ALOE

CARIBBEAN COCONUT

8 FL. OZ. / 236 mL

PRINCIPAL DISPLAY PANEL - 236 mL Bottle Label - Marshmallow Cloud

instyle
ACTIVESSENCE®

HAND
SANITIZER
SPRAY

KILLS 99.99%
OF GERMS

FAST DRYING
WITH ALOE

MARSHMALLOW CLOUD

8 FL. OZ. / 236 mL

PRINCIPAL DISPLAY PANEL - 236 mL Bottle Label - Tahitian Vanilla

instyle
ACTIVESSENCE®

HAND
SANITIZER
SPRAY

KILLS 99.99%
OF GERMS

FAST DRYING
WITH ALOE

TAHITIAN VANILLA

8 FL. OZ. / 236 mL

PRINCIPAL DISPLAY PANEL - 236 mL Bottle Label - Wild Melon

instyle
ACTIVESSENCE®

HAND
SANITIZER
SPRAY

KILLS 99.99%
OF GERMS

FAST DRYING
WITH ALOE

WILD MELON

8 FL. OZ. / 236 mL